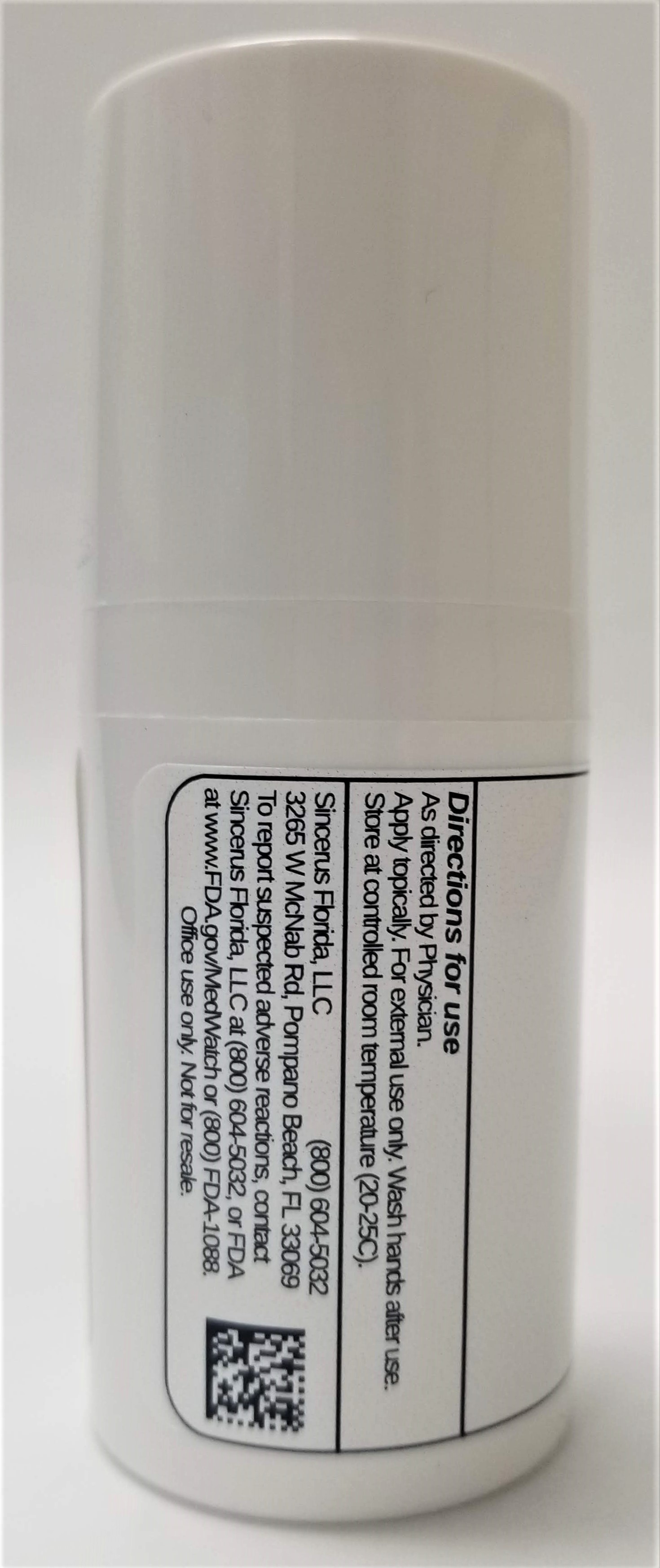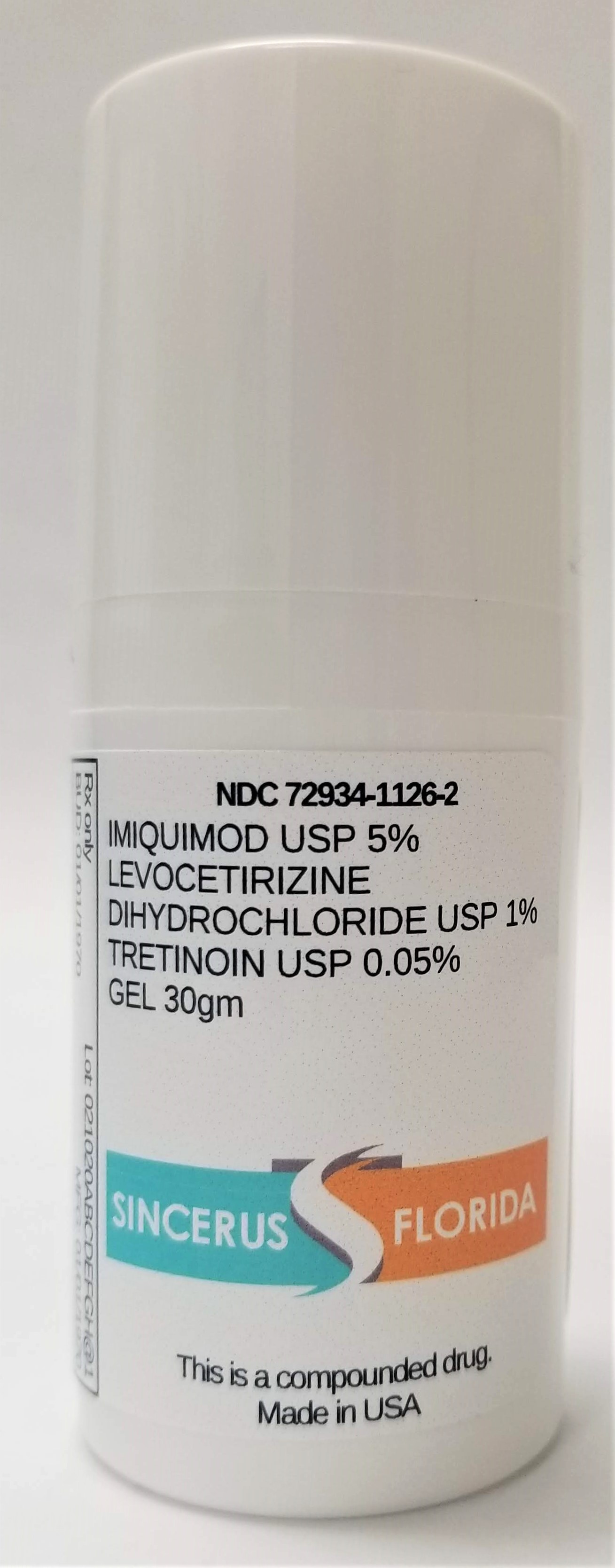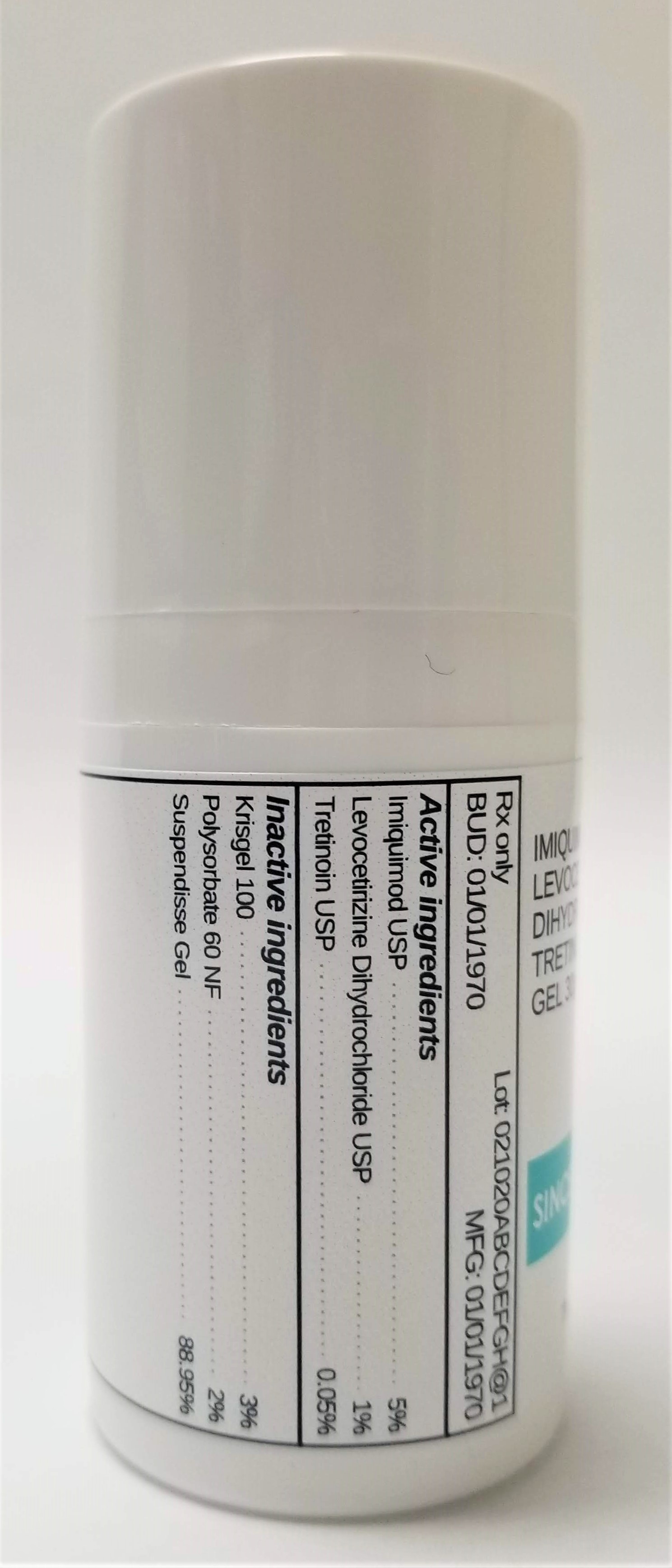 DRUG LABEL: IMIQUIMOD 5% / LEVOCETIRIZINE DIHYDROCHLORIDE 1% / TRETINOIN 0.05%
NDC: 72934-1126 | Form: GEL
Manufacturer: Sincerus Florida, LLC
Category: prescription | Type: HUMAN PRESCRIPTION DRUG LABEL
Date: 20190423

ACTIVE INGREDIENTS: TRETINOIN 0.05 g/100 g; LEVOCETIRIZINE DIHYDROCHLORIDE 1 g/100 g; IMIQUIMOD 5 g/100 g

IMIQUIMOD 5% / LEVOCETIRIZINE DIHYDROCHLORIDE 1% / TRETINOIN 0.05%